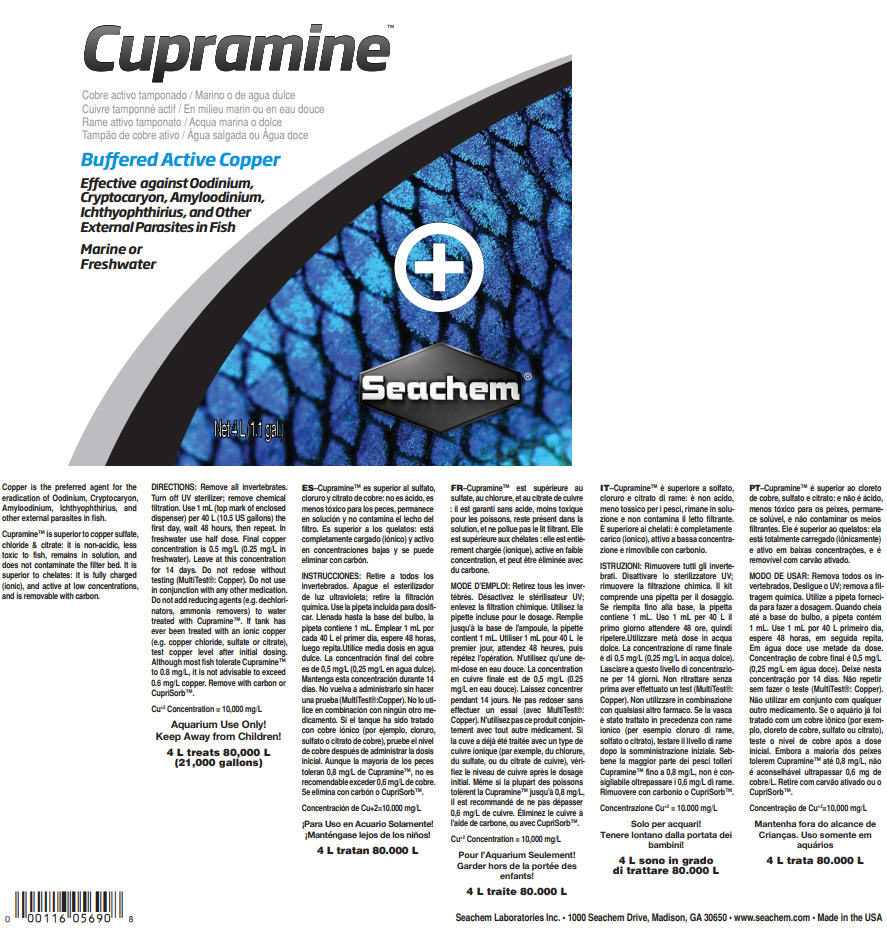 DRUG LABEL: Cupramine
NDC: 55999-057 | Form: LIQUID
Manufacturer: Seachem Laboratories Inc.
Category: animal | Type: OTC ANIMAL DRUG LABEL
Date: 20190807

ACTIVE INGREDIENTS: CUPRIC SULFATE ANHYDROUS 25.1 mg/1 mL

Cupramine™

VETERINARY INDICATIONS

Copper is the preferred agent for the eradication of Oodinium, Cryptocaryon, Amyloodinium, Ichthyophthirius, and other external parasites in fish.

Cupramine™ is superior to copper sulfate, chloride & citrate: it is non-acidic, less toxic to fish, remains in solution, and does not contaminate the filter bed. It is superior to chelates: it is fully charged (ionic), and active at low concentrations, and is removable with carbon.

DOSAGE AND ADMINISTRATION

DIRECTIONS: Remove all invertebrates. Turn off UV sterilizer; remove chemical filtration. Use 1 mL (top mark of enclosed dispenser) per 40 L (10.5 US gallons) the first day, wait 48 hours, then repeat. In freshwater use half dose. Final copper concentration is 0.5 mg/L (0.25 mg/L in freshwater). Leave at this concentration for 14 days. Do not redose without testing (MultiTest®: Copper). Do not use in conjunction with any other medication. Do not add reducing agents (e.g. dechlorinators, ammonia removers) to water treated with Cupramine™. If tank has ever been treated with an ionic copper (e.g. copper chloride, sulfate or citrate), test copper level after initial dosing. Although most fish tolerate Cupramine™ to 0.8 mg/L, it is not advisable to exceed 0.6 mg/L copper. Remove with carbon or CupriSorb™.

Cu^+2 Concentration = 10,000 mg/L

SAFE HANDLING WARNING

Aquarium Use Only!
Keep Away from Children!

4 L treats 80,000 L
(21,000 gallons)

Seachem Laboratories Inc. • 1000 Seachem Drive, Madison, GA 30650 • www.seachem.com • Made in the USA

PRINCIPAL DISPLAY PANEL - 4 L Bottle Label

Cupramine™

Buffered Active Copper

Effective against Oodinium,
Cryptocaryon, Amyloodinium,
Ichthyophthirius, and Other
External Parasites in Fish

Marine or
Freshwater

Net 4 L (1.1 gal.)

Seachem®